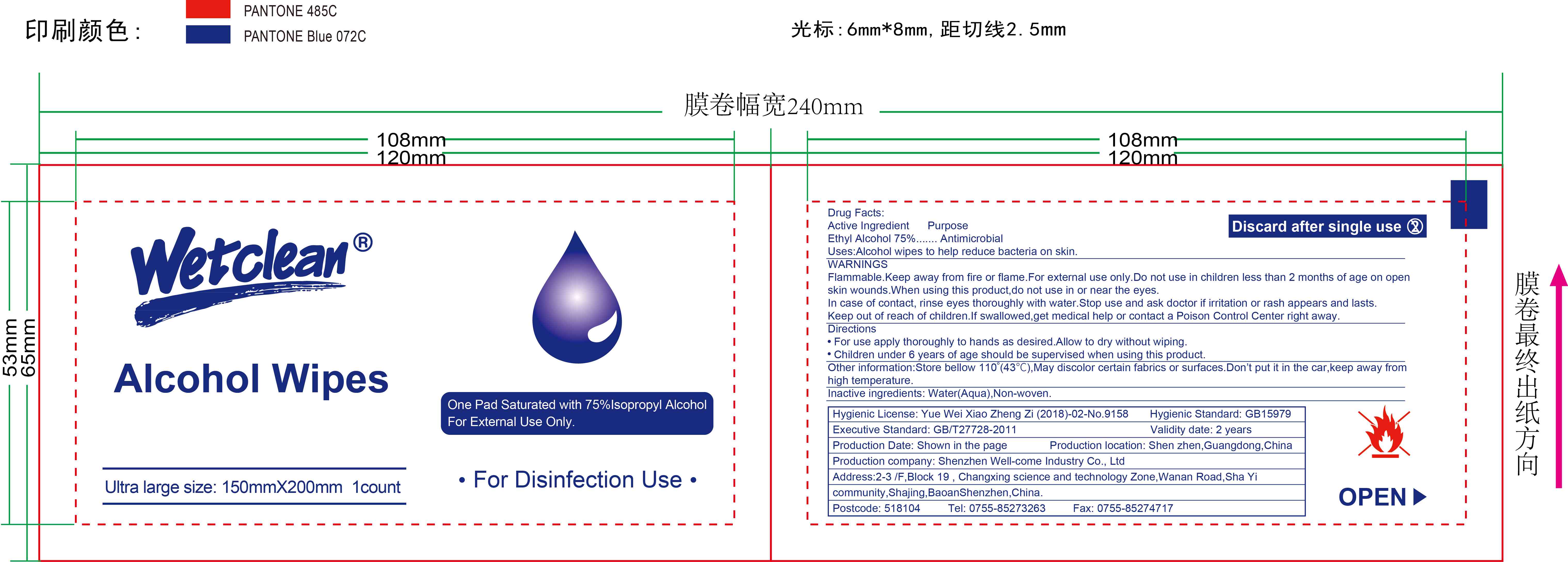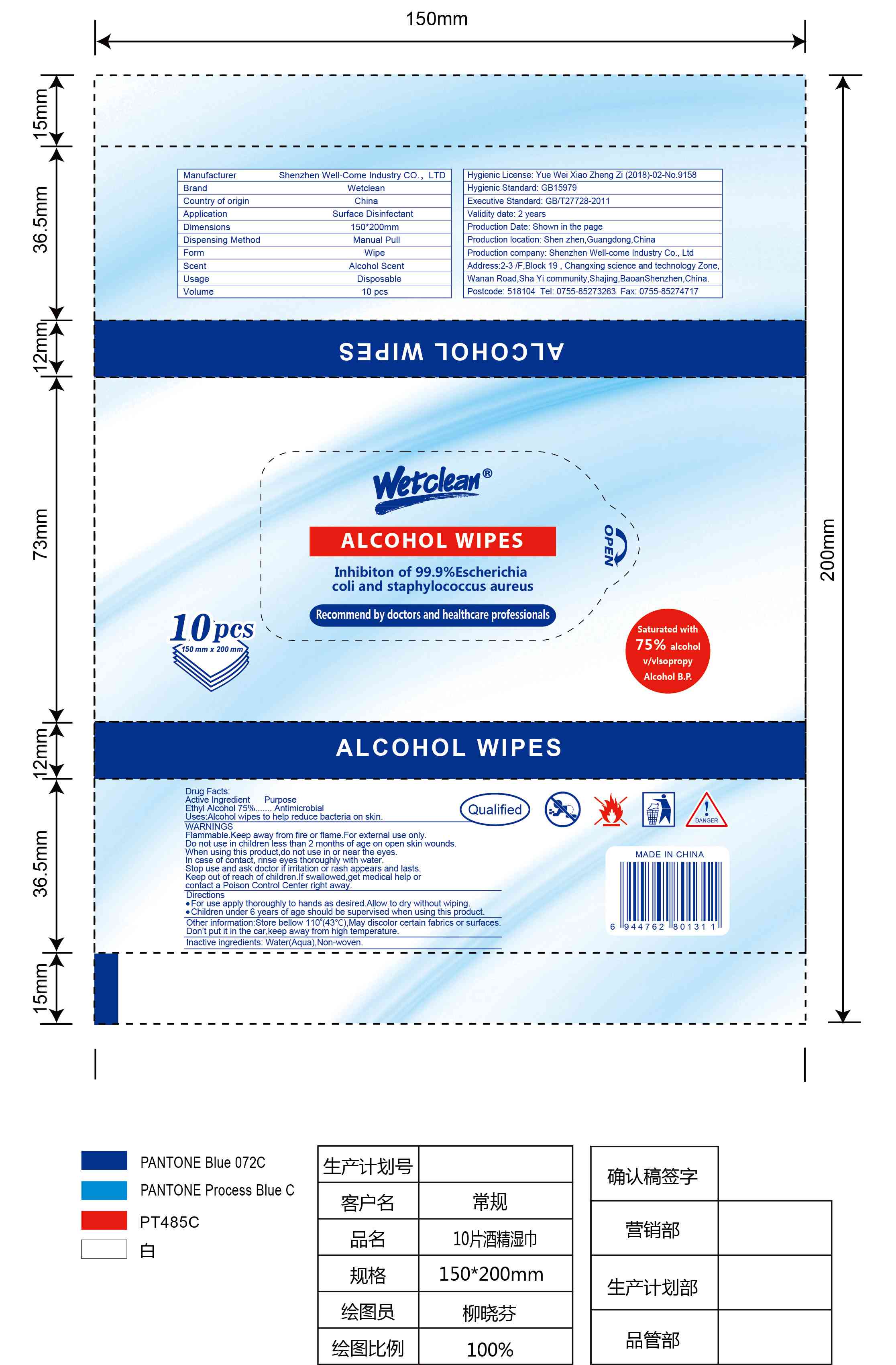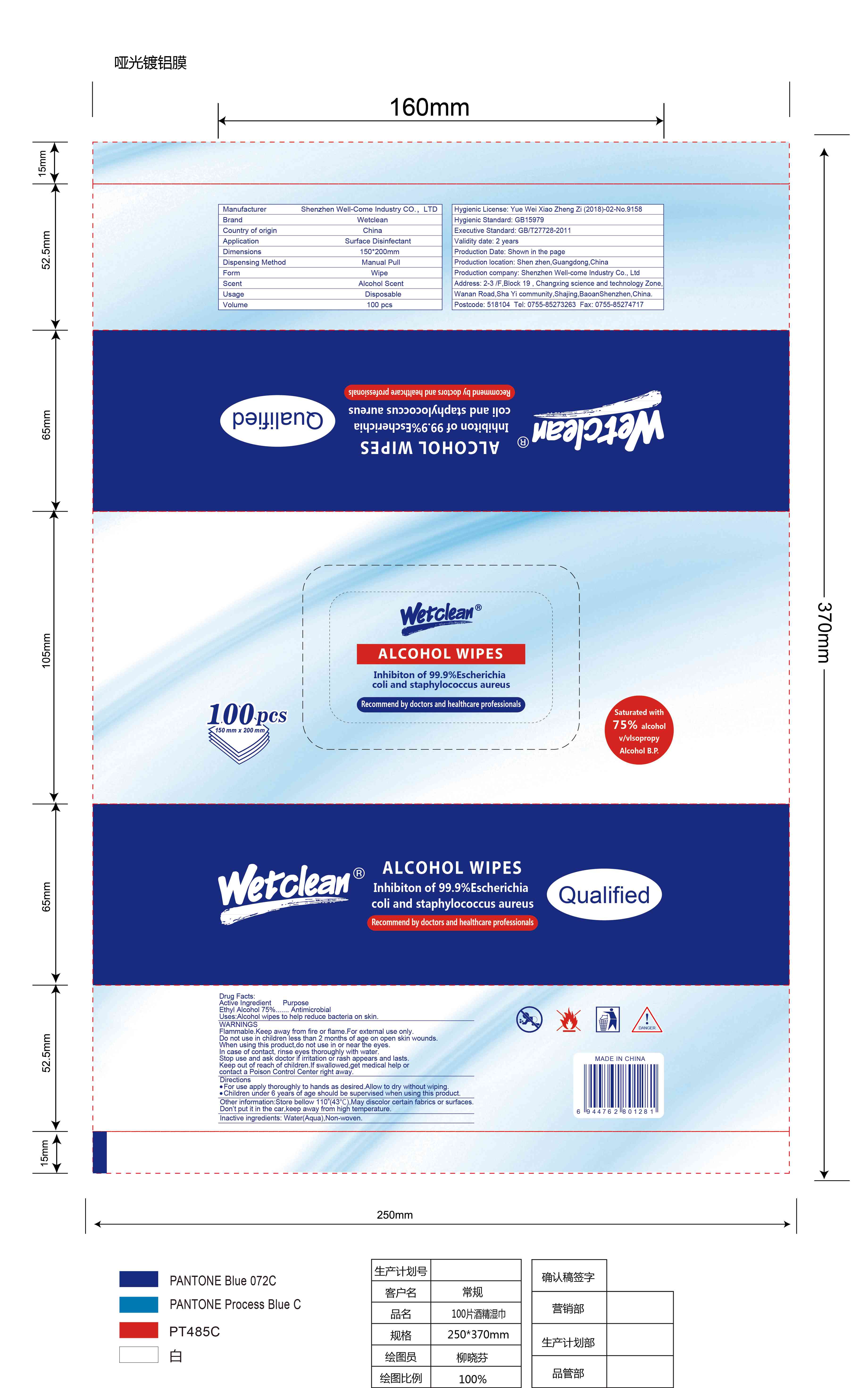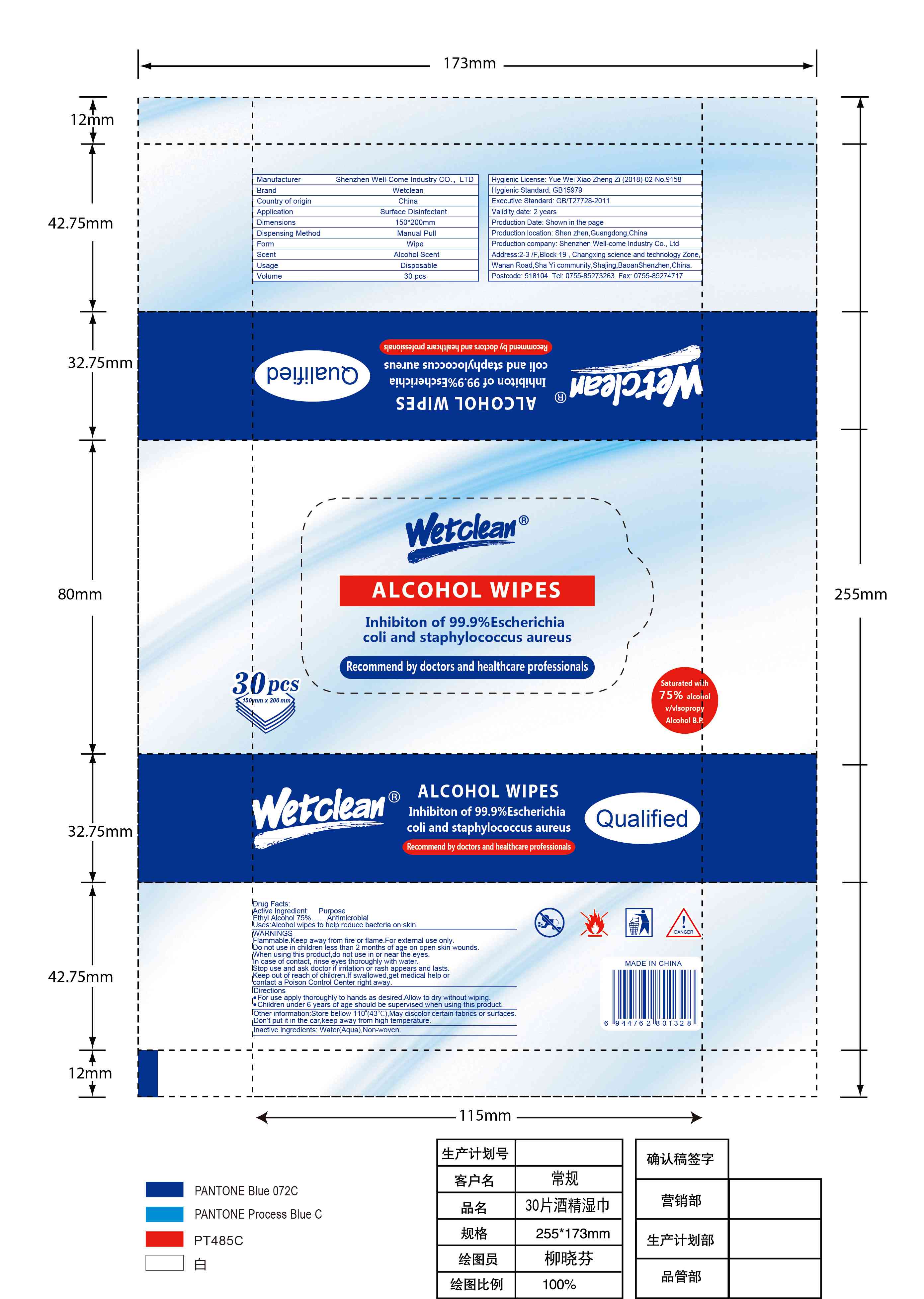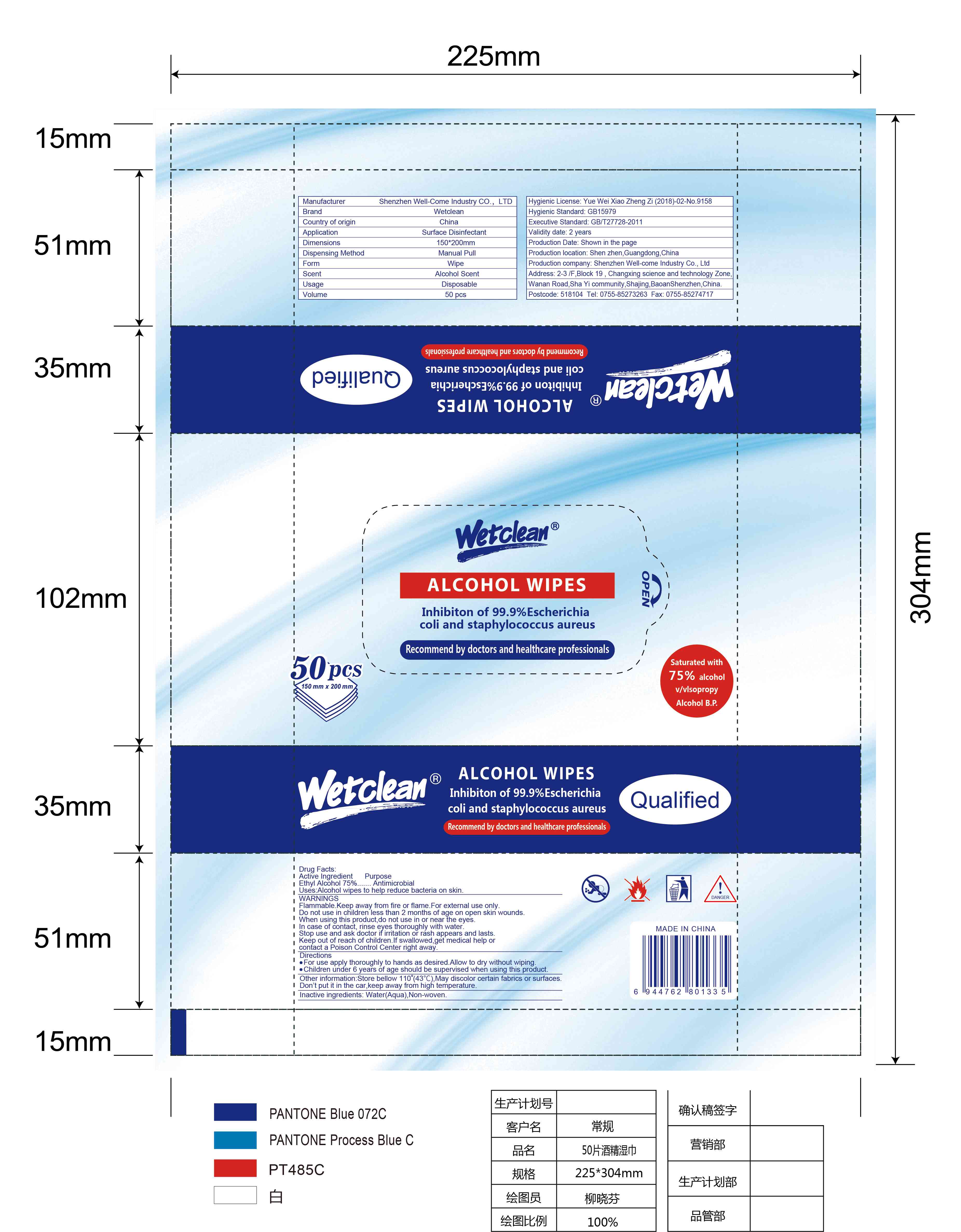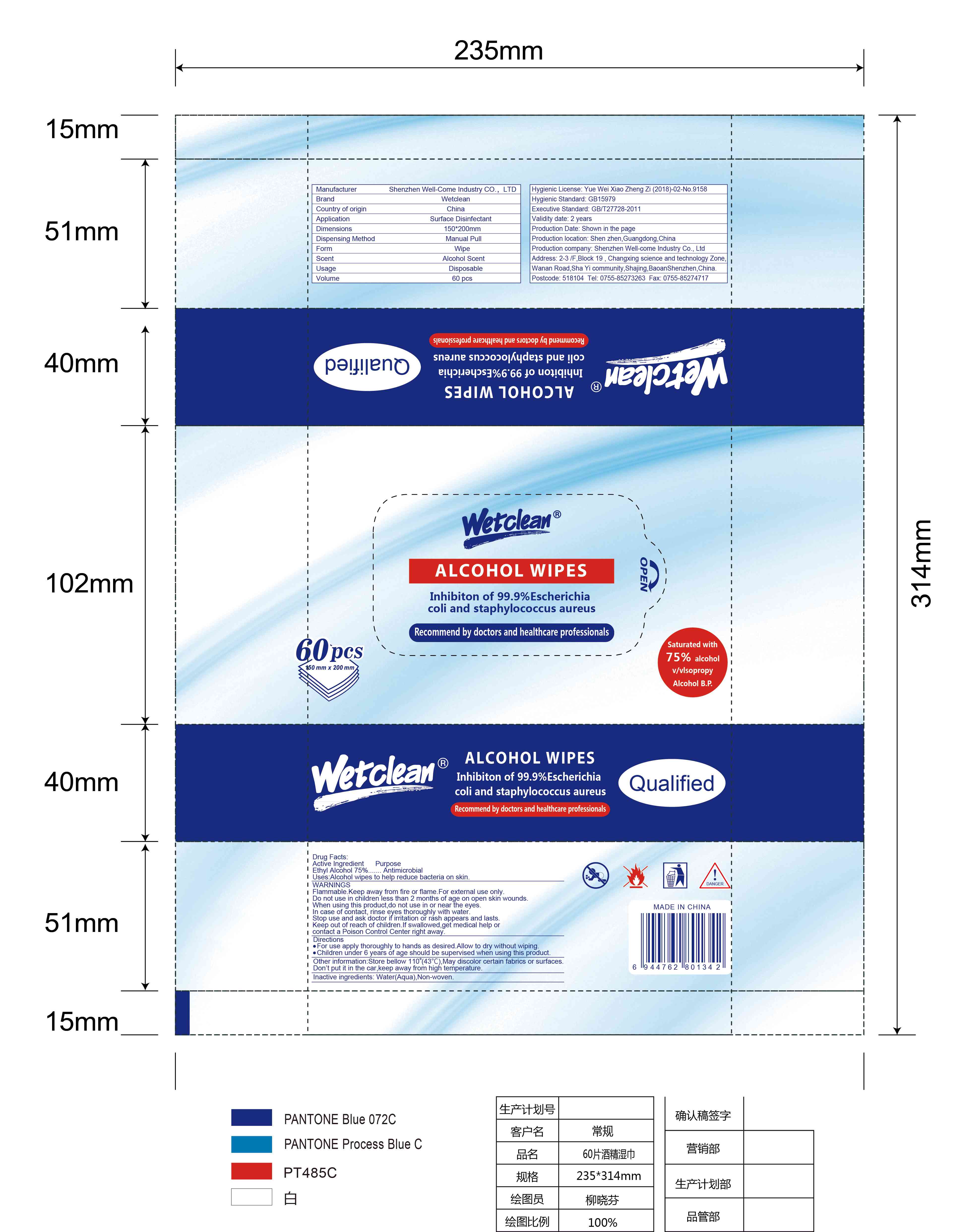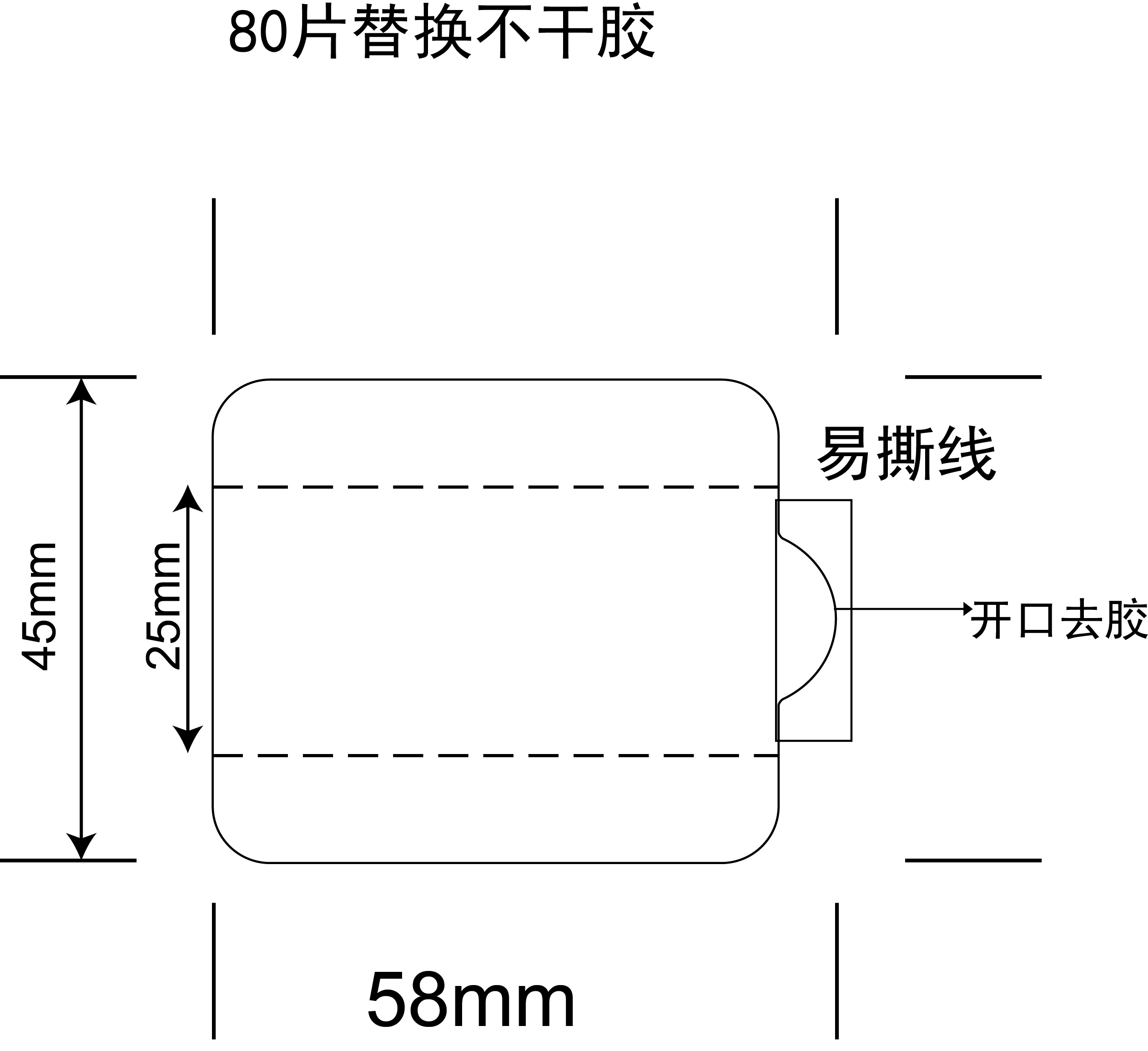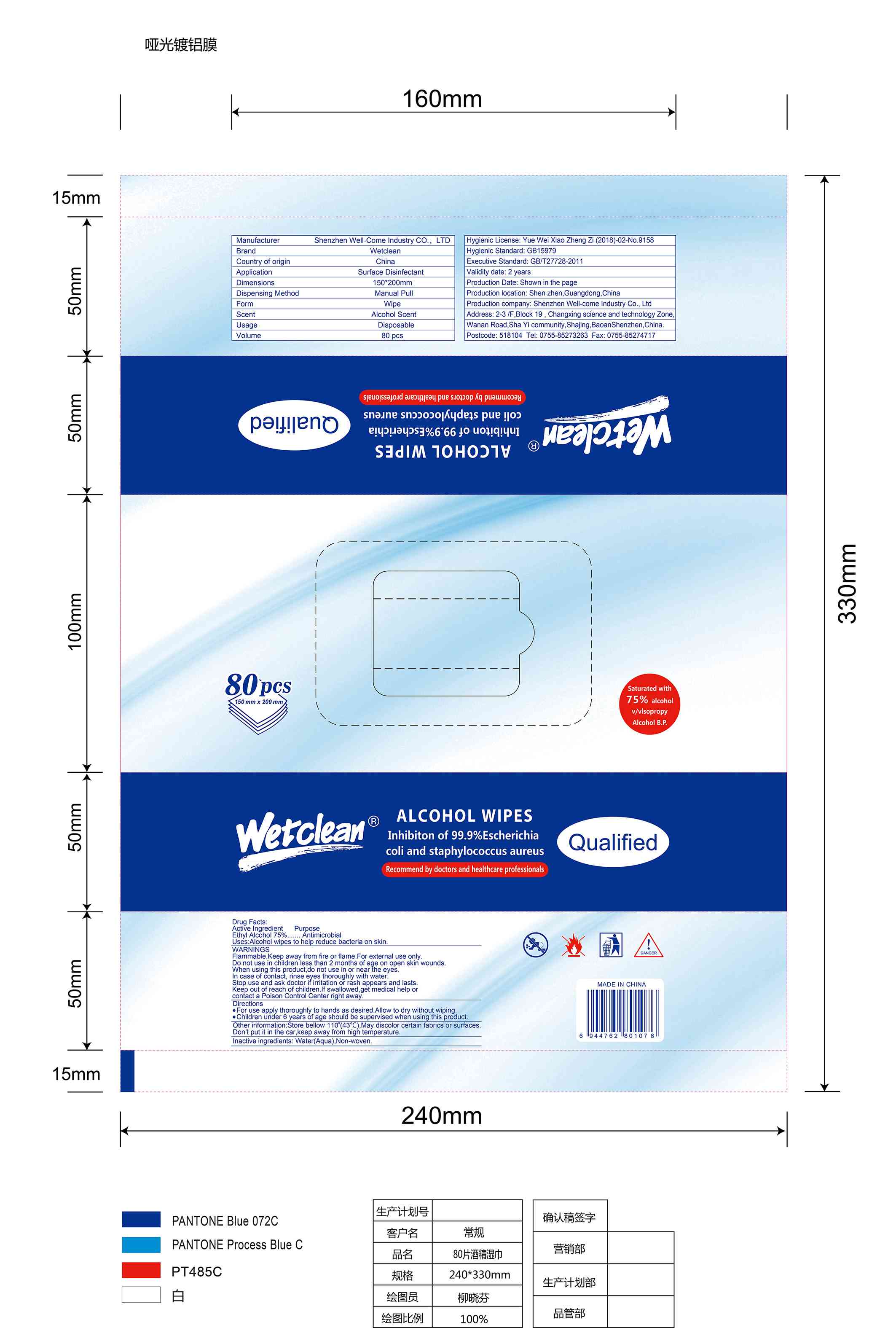 DRUG LABEL: Alcohol Wipes
NDC: 78960-001 | Form: CLOTH
Manufacturer: Shenzhen Well-Come Industry CO., LTD
Category: otc | Type: HUMAN OTC DRUG LABEL
Date: 20200709

ACTIVE INGREDIENTS: ALCOHOL 75 1/100 1
INACTIVE INGREDIENTS: WATER

Alcohol Wipes

Active Ingredient(s)

Ethyl Alcohol 75%

Purpose

Antimicrobial

Use

Alcohol wipes to help reduce bacteria on skin.

Warnings

Flammable.Keep away from fire or flame.For external use only.

Do not use in children less than 2 months of age on open skin wounds.

When using this product,do not use in or near the eyes.
In case of contact, rinse eyes thoroughly with water.

Stop use and ask doctor if irritation or rash appears and lasts.

Keep out of reach of children.If swallowed,get medical help or contact a Poison Control Center right away.

Directions

For use apply thoroughly to hands as desired.Allow to dry without wiping.
Children under 6 years of age should be supervised when using this product.

Other information

Store bellow 110°(43°C),May discolor certain fabrics or surfaces. Don't put it in the car,keep away from high temperature.

Inactive ingredients

Water(Aqua),Non-woven.